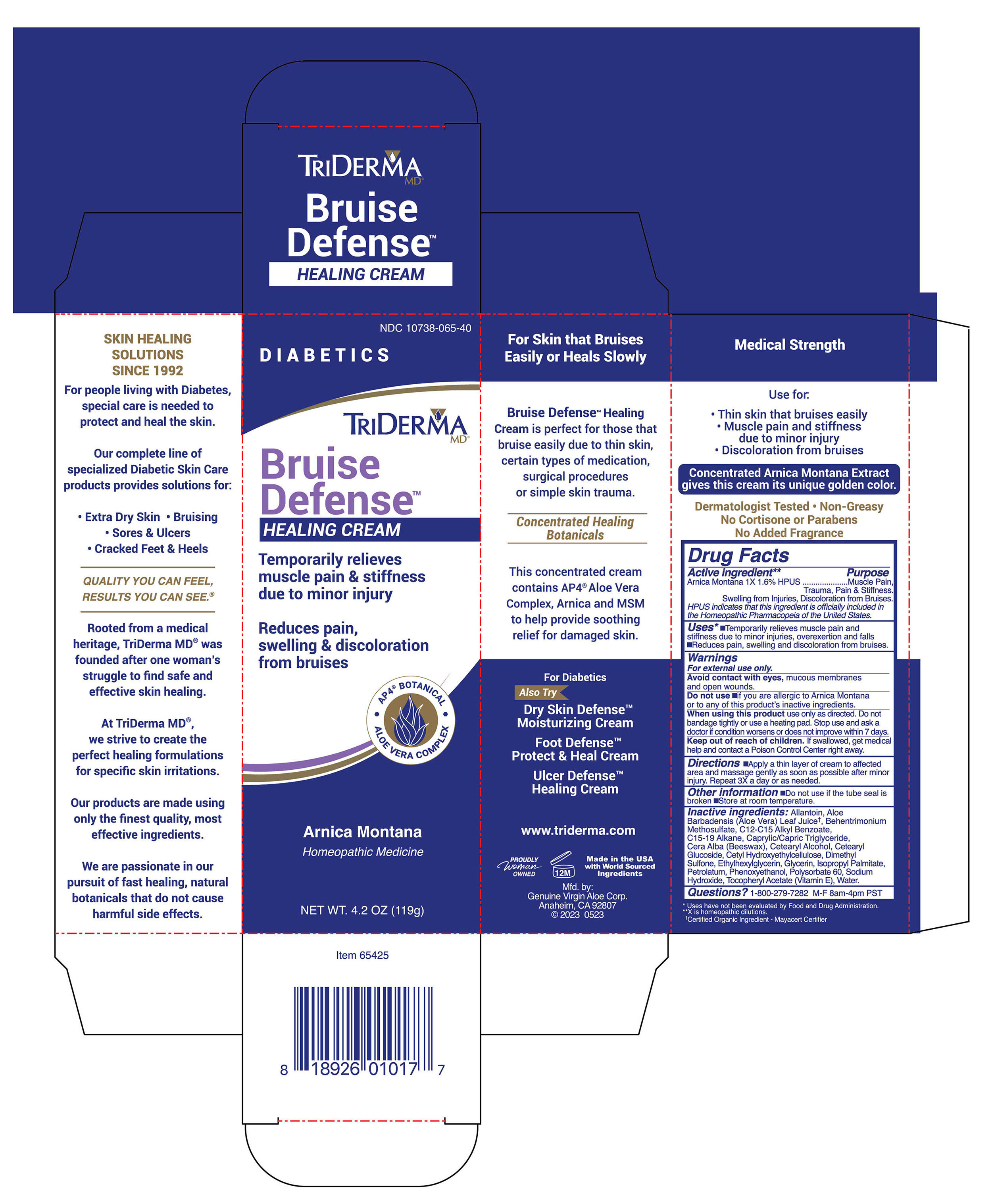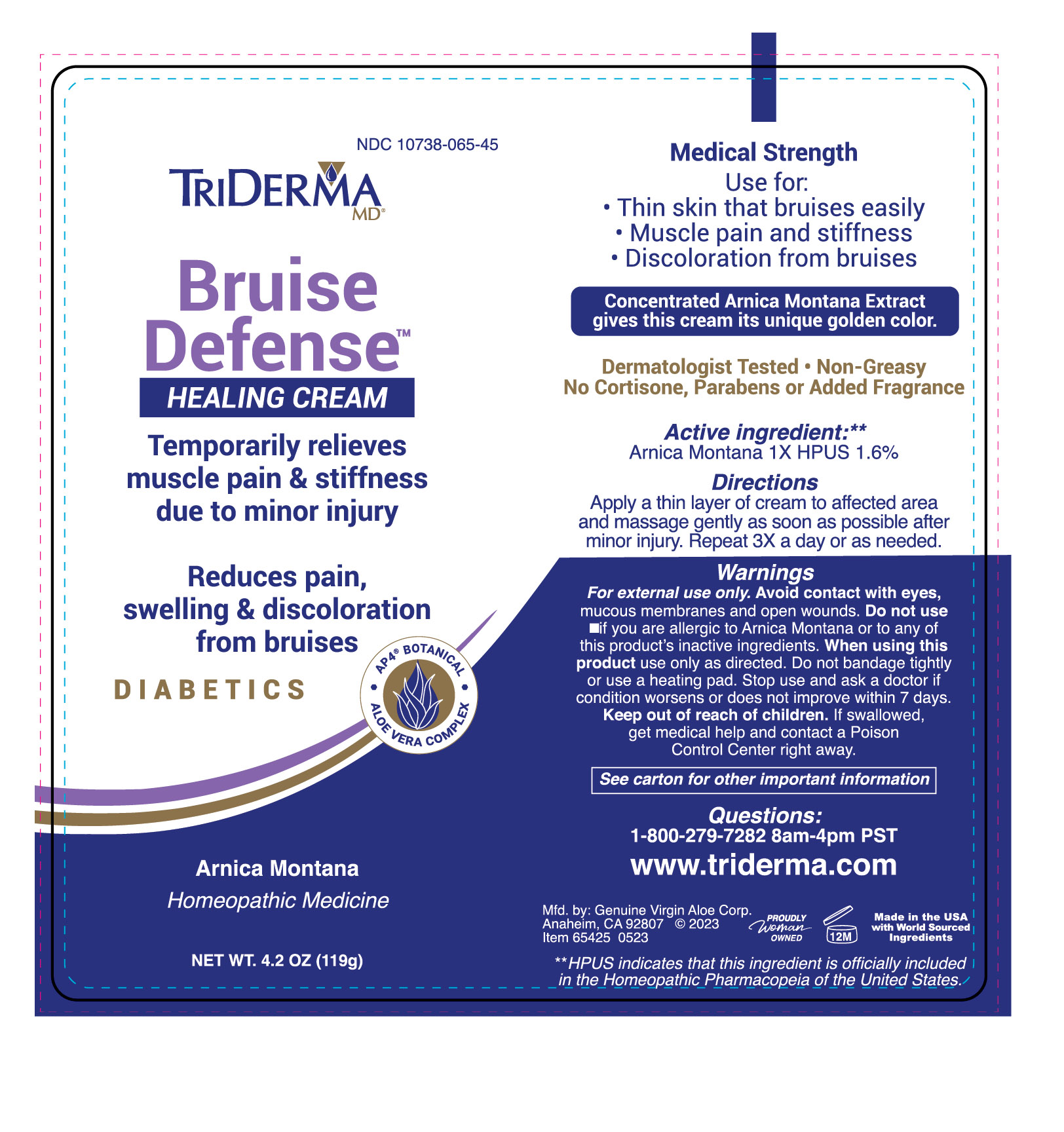 DRUG LABEL: TRIDERMA BRUISE DEFENSE HEALING -DIABETICS
NDC: 10738-065 | Form: CREAM
Manufacturer: Genuine Virgin Aloe Corporation
Category: homeopathic | Type: HUMAN OTC DRUG LABEL
Date: 20260128

ACTIVE INGREDIENTS: ARNICA MONTANA FLOWER 1.6 g/100 g
INACTIVE INGREDIENTS: PETROLATUM; WATER; DIMETHYL SULFONE; ISOPROPYL PALMITATE; MEDIUM-CHAIN TRIGLYCERIDES; GLYCERIN; CETOSTEARYL ALCOHOL; WHITE WAX; POLYSORBATE 60; .ALPHA.-TOCOPHEROL ACETATE; ALKYL (C12-15) BENZOATE; ALOE VERA LEAF; ALLANTOIN; HYDROXYETHYL CELLULOSE (100 MPA.S AT 2%); SODIUM HYDROXIDE; PHENOXYETHANOL; ETHYLHEXYLGLYCERIN; BEHENTRIMONIUM METHOSULFATE; C15-19 ALKANE; CETEARYL GLUCOSIDE

TRIDERMA Bruise Defense Healing Cream

Active ingredient

Arnica Montana Flower Extract 1X 1.60% HPUS

Purpose

Muscle pain, trauma, pain & stiffness, swelling from injuries, discoloration from bruises

HPUS indicates that this ingredient officially included in the Homeopathic Pharmacopeia of the United States.

INDICATIONS AND USAGE

Uses •Temporarily relieves muscle pain and stiffness due to minor injuries, overexertion and falls •Reduces pain, swelling and discoloration from bruises

Warnings For external use only.

Avoid contact with eyes, mucous membranes, damaged skin and wounds.

Do not use •if you are allergic to Arnica Montana or to any of this product’s inactive ingredients.

When using this product use only as directed. Do not bandage tightly or use a heating pad. Stop use and ask a doctor if condition persists for more than 7 days or worsens.

Keep out of reach of children. If swallowed, get medical help and contact a Poison Control Center right away.

DOSAGE AND ADMINISTRATION

Directions •Apply a thin layer of cream to affected area and massage gently as soon as possible after minor injury. Repeat 3X a day or as needed.

Other Information •Do not use if glued carton end flaps are open or if the tube seal is broken. •Non-greasy, store at 20-25°C.

INACTIVE INGREDIENT

Inactive ingredients: Allantoin, Aloe Barbadensis (Aloe Vera) Leaf Juice†, Behentrimonium Methosulfate, C12-C15 Alkyl Benzoate, C15-19 Alkane, Caprylic/Capric Triglyceride, Cera Alba (Beeswax), Cetearyl Alcohol, Cetearyl Glucoside, Cetyl Hydroxyethylcellulose, Dimethyl Sulfone, Ethylhexylglycerin, Glycerin, Isopropyl Palmitate, Petrolatum, Phenoxyethanol, Polysorbate 60, Sodium Hydroxide, Tocopheryl Acetate (Vitamin E), Water.†Certified Organic Ingredient - Mayacert Certifier

QUESTIONS

Questions? 1-800-279-7282 M-F 8am-4pm PST

Temporarily relieves muscle pain & stiffness due to minor injury

Reduces pain, swelling & discoloration

AP4® BOTANICAL

ALOE VERA COMPLEX

with Arnica Montana

Homeopathic Medicine

For Skin that Bruises Easily or Heals Slowly

Bruise Defense™ Healing Cream helps promote the appearance of healthy skin and faster healing from bruising due to certain types of medication, surgical procedures or simple skin trauma.

Maximum Strength Healing Botanicals

This concentrated cream contains AP4® Botanical Aloe Complex, Arnica and MSM to help provide soothing relief for damaged skin.

CERTIFIED ORGANIC ALOE

LEARN MORE @ triderma

www.triderma.com

MADE IN THE USA

Mfd. by: Genuine Virgin Aloe Corp. Anaheim, CA 92807

Helps Relieve:

• Muscle pain and stiffness

• Swelling from minor injury

• Reduces discoloration from bruises

Non-Greasy • No Cortisone Or Parabens

No Added Fragrance

- Uses have not been evaluated by Food and Drug Administration.

- X is homeopathic dilutions.

For people living with Diabetes, special care is needed to protect and heal the skin. Our line of specialized Diabetic products, Foot Defense™, Dry Skin Defense™ and Ulcer Defense™ helps provide a solution for these special skin problems.

Quality you can feel, results you can see.®

Rooted from a medical heritage, TriDerma MD® was founded after one woman’s struggle to find safe and effective skin healing.

At TriDerma MD®, we strive to create the perfect healing formulations for specific skin irritations. Our products are made using only the finest quality, most effective ingredients.

We are passionate in our pursuit of fast healing, natural botanicals that do not cause harmful side effects.